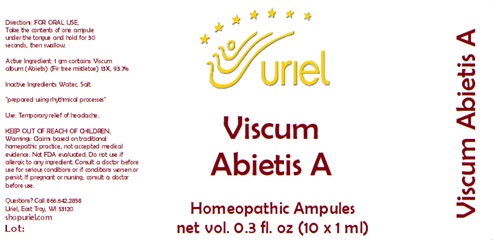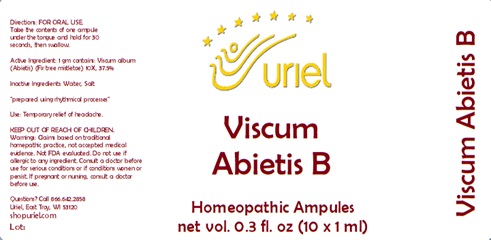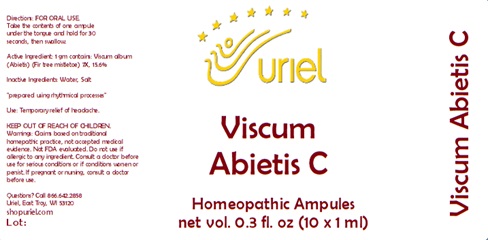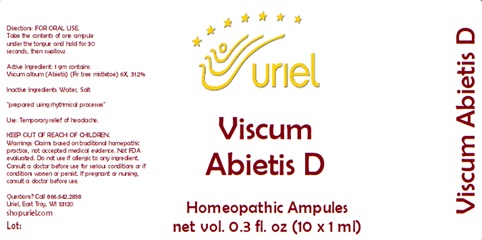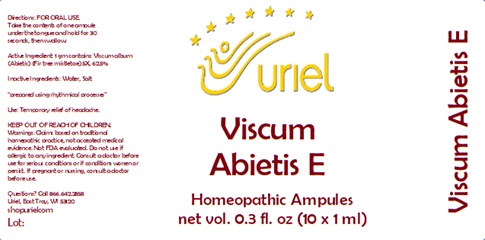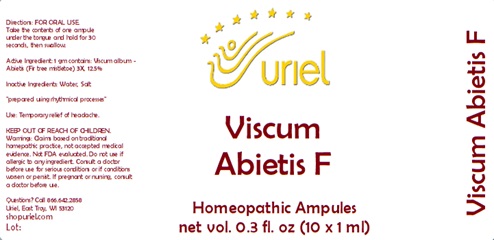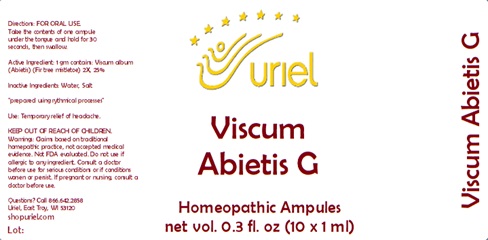 DRUG LABEL: Viscum Abietis
NDC: 48951-1001 | Form: LIQUID
Manufacturer: Uriel Pharmacy Inc
Category: homeopathic | Type: HUMAN OTC DRUG LABEL
Date: 20240221

ACTIVE INGREDIENTS: VISCUM ALBUM FRUITING TOP 2 [hp_X]/1 mL
INACTIVE INGREDIENTS: WATER; SODIUM CHLORIDE

Viscum Abietis Homeopathic Ampules

INDICATIONS AND USAGE

Directions: FOR ORAL USE.

DOSAGE AND ADMINISTRATION

Take the contents of one ampule under the tongue and hold for 30 seconds, then swallow.

Active Ingredient:Viscum album - Abietis (Fir tree mistletoe) | 1 gm contains:
A | 13X 93.7%
B | 10X 37.5%
C | 7X 15.6%
D | 6X 31.2%
E | 5X 62.5%
F | 3X 12.5%
G | 2X 25%

Inactive Ingredients: Water, Salt

"prepared using rhythmical processes"

PURPOSE

Use: Temporary relief of headache.

KEEP OUT OF REACH OF CHILDREN.

WARNINGS

Warnings: Claims based on traditional homepathic practice, not accepted medical evidence. Not FDA evaluated. Do not use if allergic to any ingredient. Consult a doctor before use for serious conditions or if conditions worsen or persist. If pregnant or nursing, consult a doctor before use.

Questions? Call 866 642-2858

Uriel, East Troy, WI 53120

shopuriel.com Lot: